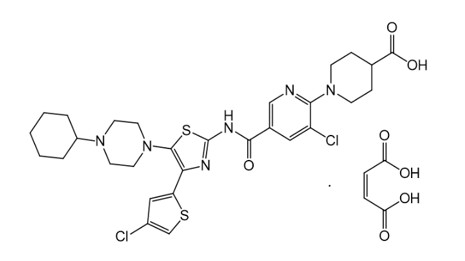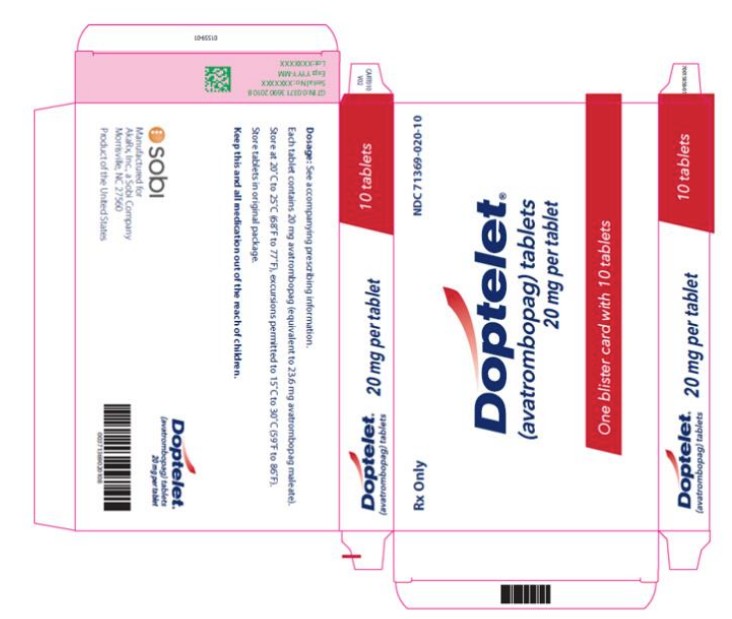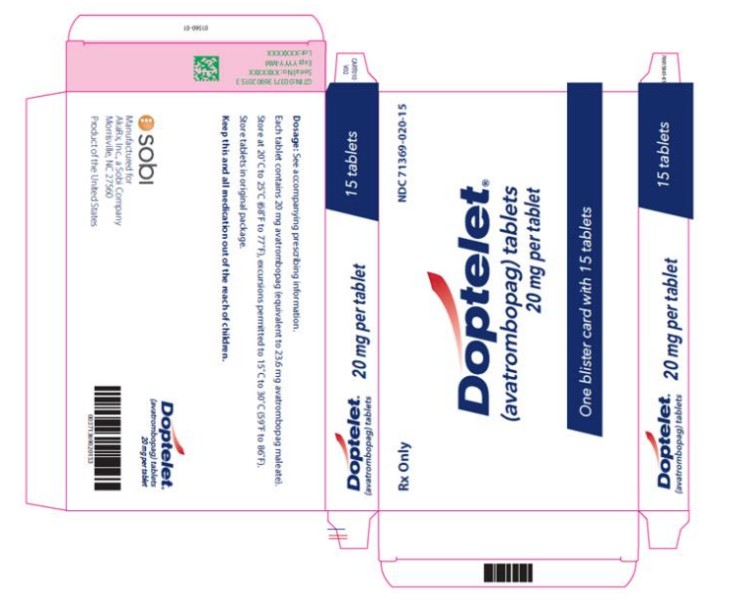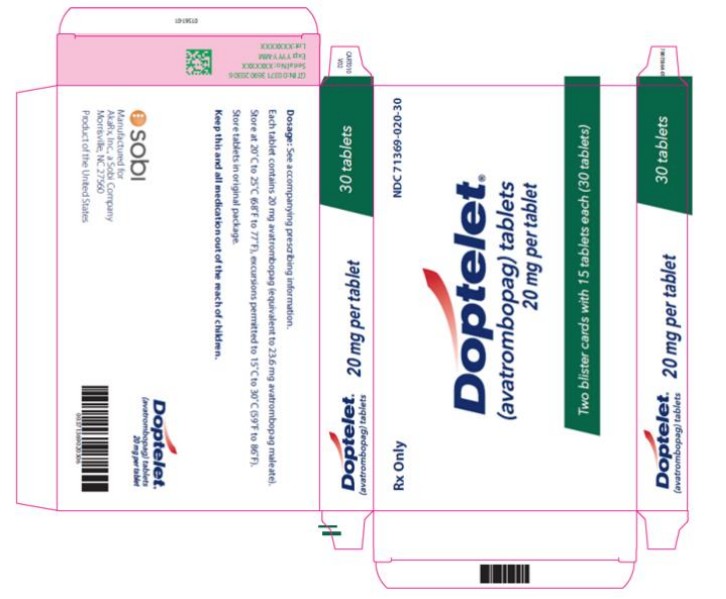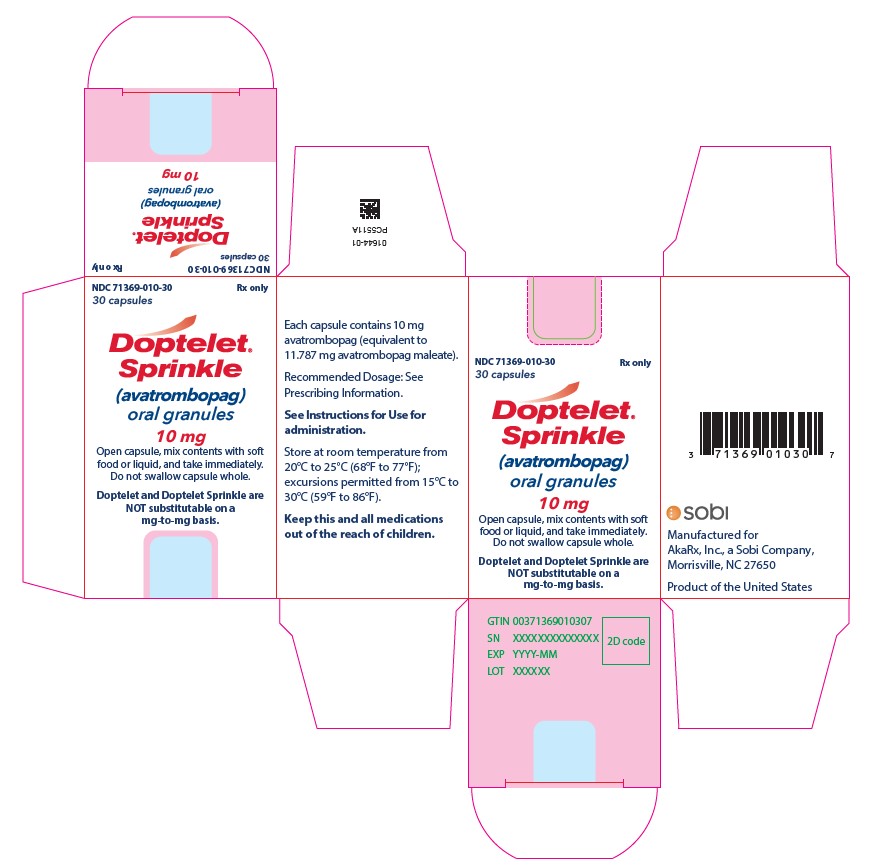 DRUG LABEL: DOPTELET
NDC: 71369-020 | Form: TABLET, FILM COATED
Manufacturer: AkaRx, Inc.
Category: prescription | Type: HUMAN PRESCRIPTION DRUG LABEL
Date: 20250813

ACTIVE INGREDIENTS: AVATROMBOPAG MALEATE 20 mg/1 1
INACTIVE INGREDIENTS: LACTOSE MONOHYDRATE; SILICON DIOXIDE; CROSPOVIDONE; MAGNESIUM STEARATE; MICROCRYSTALLINE CELLULOSE; POLYVINYL ALCOHOL, UNSPECIFIED; TALC; POLYETHYLENE GLYCOL, UNSPECIFIED; TITANIUM DIOXIDE; FERRIC OXIDE YELLOW

HIGHLIGHTS OF PRESCRIBING INFORMATION

These highlights do not include all the information needed to use DOPTELET safely and effectively. See full prescribing information for DOPTELET.
DOPTELET® (avatrombopag) tablets, for oral use
DOPTELET® SPRINKLE (avatrombopag) oral granules
Initial U.S. Approval: 2018

RECENT MAJOR CHANGES

Indications and Usage (1.3) 07/2025

Dosage and Administration (2.1, 2.3, 2.4, 2.5, 2.6, 2.7, 2.8) 07/2025

Warnings and Precautions (5.1) 07/2024

1 INDICATIONS AND USAGE

DOPTELET is a thrombopoietin receptor agonist indicated for the treatment of:

- Thrombocytopenia in adult patients with chronic liver disease who are scheduled to undergo a procedure. (1.1)
- Thrombocytopenia in adult patients with chronic immune thrombocytopenia who have had an insufficient response to a previous treatment. (1.2)
- Thrombocytopenia in pediatric patients 1 year and older with persistent or chronic immune thrombocytopenia who have had an insufficient response to a previous treatment (1.3)

2 DOSAGE AND ADMINISTRATION

- DOPTELET tablets and DOPTELET SPRINKLE are not substitutable on a mg-to-mg basis.
- DOPTELET SPRINKLE capsules should be opened, and the contents (oral granules) mixed with a soft food or liquid. Administer immediately after mixing. Do not swallow the capsules whole.
- Administer DOPTELET tablets and DOPTELET SPRINKLE with food. (2.1, 2.3, 2.5)
- Chronic Liver Disease: Dose DOPTELET tablets based upon platelet count prior to procedure, orally for 5 days beginning 10 days to 13 days before procedure. For platelet count less than 40×10^9/L, the dose is 60 mg (3 tablets) orally once daily; for platelet count 40 to less than 50×10^9/L the dose is 40 mg (2 tablets) orally once daily. (2.2)
- Adult Patients with Chronic Immune Thrombocytopenia and Pediatric Patients 6 Years and Older with Persistent or Chronic Immune Thrombocytopenia: Initiate DOPTELET tablets at 20 mg (1 tablet) orally once daily. Adjust the dose or frequency of dosing to maintain platelet count greater than or equal to 50×10^9/L. Do not exceed 40 mg (2 tablets) per day.
- Pediatric Patients 1 Year to Less than 6 Years with Persistent or Chronic Immune Thrombocytopenia: Initiate DOPTELET SPRINKLE oral granules at 10 mg (content of 1 capsule) orally once daily. Adjust the dose or frequency of dosing to maintain platelet count greater than or equal to 50×10^9/L. Do not exceed 20 mg (content of 2 capsules) per day.

3 DOSAGE FORMS AND STRENGTHS

Tablet: 20 mg (3)

Oral Granules: 10 mg (3)

4 CONTRAINDICATIONS

None. (4)

5 WARNINGS AND PRECAUTIONS

Thrombotic/Thromboembolic Complications: DOPTELET is a thrombopoietin (TPO) receptor agonist and TPO receptor agonists have been associated with thrombotic and thromboembolic complications in patients with chronic liver disease or immune thrombocytopenia.

Monitor platelet counts. Monitor for signs and symptoms of thromboembolic events and institute treatment promptly. (5.1)

6 ADVERSE REACTIONS

In adult patients with chronic liver disease, the most common adverse reactions (≥3%) were pyrexia, abdominal pain, nausea, headache, fatigue, and edema peripheral. (6.1)

In adult patients with chronic immune thrombocytopenia, the most common adverse reactions (≥10%) were headache, fatigue, contusion, epistaxis, upper respiratory tract infection, arthralgia, gingival bleeding, petechiae and nasopharyngitis. (6.1)

In pediatric patients with persistent or chronic immune thrombocytopenia, the most common adverse reactions (≥10%) were viral infection, nasopharyngitis, cough, pyrexia, and oropharyngeal pain. (6.1)

To report SUSPECTED ADVERSE REACTIONS, contact Sobi, Inc. at 1-866-773-5274 or FDA at 1-800-FDA-1088 or www.fda.gov/medwatch.

7 DRUG INTERACTIONS

Moderate or Strong Dual CYP2C9 and CYP3A4 Inducers or Inhibitors: Dose adjustments are recommended for patients with persistent or chronic immune thrombocytopenia. (7.1)

8 USE IN SPECIFIC POPULATIONS

- Pregnancy: May cause fetal harm (8.1)
- Lactation: Advise not to breastfeed. (8.2)

FULL PRESCRIBING INFORMATION

1 INDICATIONS AND USAGE

1.1 Treatment of Thrombocytopenia in Patients with Chronic Liver Disease (CLD)

DOPTELET is indicated for the treatment of thrombocytopenia in adult patients with chronic liver disease who are scheduled to undergo a procedure.

1.2 Treatment of Thrombocytopenia in Adult Patients with Chronic Immune Thrombocytopenia (ITP)

DOPTELET is indicated for the treatment of thrombocytopenia in adult patients with chronic immune thrombocytopenia who have had an insufficient response to a previous treatment.

1.3 Treatment of Thrombocytopenia in Pediatric Patients 1 Year and Older with Persistent or Chronic Immune Thrombocytopenia (ITP)

DOPTELET is indicated for the treatment of thrombocytopenia in pediatric patients 1 year and older with persistent or chronic immune thrombocytopenia who have had an insufficient response to a previous treatment.

2 DOSAGE AND ADMINISTRATION

2.1 Important Use and Administration Instructions

- Select the recommended product (DOPTELET tablets or DOPTELET SPRINKLE) based on the indication and patient’s age.
- Administer DOPTELET tablets and DOPTELET SPRINKLE with food.
- DOPTELET tablets and DOPTELET SPRINKLE are not substitutable on a mg-to-mg basis.
- The mixture prepared from the granules in DOPTELET SPRINKLE capsules is more bioavailable than DOPTELET tablets [see Clinical Pharmacology (12.3)]. There is no experience from clinical trials in switching between dosing with the granules and the tablet. If the formulation is switched, monitor platelet counts weekly until stable platelet counts are obtained and adjust dosing as needed before resuming monthly monitoring.

2.2 Recommended Dosage of DOPTELET Tablets for Patients with Chronic Liver Disease

Begin DOPTELET tablets dosing 10 days to 13 days prior to the scheduled procedure. The recommended daily dose of DOPTELET is based on the patient’s platelet count prior to the scheduled procedure (see Table 1). Patients should undergo their procedure 5 days to 8 days after the last dose of DOPTELET.

DOPTELET tablets should be taken orally once daily for 5 consecutive days with food. All 5 days of dosing should be completed.

Table 1: Recommended DOPTELET Tablets Dosage and Duration in Patients with Chronic Liver Disease Scheduled to Undergo a Procedure

Platelet Count | Recommended DOPTELET Dosage | Duration
Less than 40×10^9/L | 60 mg (3 tablets) orally once daily | 5 days
40×10^9/L to less than 50×10^9/L | 40 mg (2 tablets) orally once daily | 5 days

DOPTELET tablets have been investigated only as a single 5-day once daily dosing regimen in clinical trials in patients with chronic liver disease [see Clinical Studies (14.1)]. DOPTELET should not be administered to patients with chronic liver disease in an attempt to normalize platelet counts.

Monitoring: Obtain a platelet count prior to administration of DOPTELET therapy and on the day of a procedure to ensure an adequate increase in platelet count.

2.3 Recommended Dosage of DOPTELET Tablets for Adult Patients with Chronic Immune Thrombocytopenia and Pediatric Patients 6 Years and Older with Persistent or Chronic Immune Thrombocytopenia

Use the lowest dose of DOPTELET needed to achieve and maintain a platelet count greater than or equal to 50×10^9/L as necessary to reduce the risk for bleeding. Dose adjustments are based on platelet count response. Do not use DOPTELET to normalize platelet counts.

Initial Dosage:

- Begin DOPTELET tablets at an initial dosage of 20 mg (1 tablet) orally once daily with food (see Table 3).
- The recommended initial dosages of DOPTELET tablets are different for patients receiving certain concomitant medications (see Table 4).

Monitoring: After initiating therapy with DOPTELET, assess platelet counts weekly until a stable platelet count greater than or equal to 50×10^9/L has been achieved, and then obtain platelet counts monthly thereafter. Obtain platelet counts weekly for at least 4 weeks following discontinuation of DOPTELET.

Dose Adjustments:

DOPTELET tablet dose adjustments (see Table 2 and Table 3) are based on the platelet count response. Do not exceed a DOPTELET daily dose of 40 mg (2 tablets).

Table 2: DOPTELET Tablets Recommended Dose Adjustments for Adult Patients with Chronic Immune Thrombocytopenia and Pediatric Patients 6 Years and Older with Persistent or Chronic Immune Thrombocytopenia

Platelet Count | Dose Adjustment or Action
Less than 50×10^9/L after at least 2 weeks of DOPTELET tablets | - Increase One Dose Level per Table 3. - Wait 2 weeks to assess the effects of this regimen and any subsequent dose adjustments.
Between 200×10^9/L and 400×10^9/L | - Decrease One Dose Level per Table 3. - Wait 2 weeks to assess the effects of this regimen and any subsequent dose adjustments.
Greater than 400×10^9/L | - Stop DOPTELET tablets. - Increase platelet monitoring to twice weekly. - When platelet count is less than 150×10^9/L, decrease One Dose Level per Table 3 and reinitiate therapy.
Less than 50×10^9/L after 4 weeks of DOPTELET 40 mg (2 tablets) once daily | - Discontinue DOPTELET tablets.
Greater than 400×10^9/L after 2 weeks of DOPTELET 20 mg (1 tablet) weekly | - Discontinue DOPTELET tablets.

Table 3: DOPTELET Tablet Dose Levels for Titration in Adult Patients with Chronic Immune Thrombocytopenia and Pediatric Patients 6 Years and Older with Persistent or Chronic Immune Thrombocytopenia

Dosage | Dose Level
40 mg (2 tablets) orally Once Daily | 6
40 mg (2 tablets) orallyThree Times a Week AND 20 mg (1 tablet) orally on the Four Remaining Days of Each Week | 5
20 mg (1 tablet) orally Once Daily* | 4
20 mg (1 tablet) orally Three Times a Week | 3
20 mg (1 tablet) orally Twice a Week OR 40 mg Once Weekly | 2
20 mg (1 tablet) orally Once Weekly | 1

*Initial dosage regimen for all patients except those taking Moderate or Strong Dual Inducers or Moderate or Strong Dual Inhibitors of CYP2C9 and CYP3A4.

Discontinuation:

- Discontinue DOPTELET tablets if the platelet count does not increase to greater than or equal to 50×10^9/L after 4 weeks of dosing at the maximum dose of 40 mg (2 tablets) once daily.
- Discontinue DOPTELET tablets if the platelet count is greater than 400×10^9/L after 2 weeks of dosing at 20 mg (1 tablet) once weekly.

2.4 Recommended Initial Dosage of DOPTELET Tablets with Concomitant Moderate or Strong Dual Inducers or Inhibitors of CYP2C9 and CYP3A4

The recommended initial dosages of DOPTELET tablets with concomitant moderate or strong dual inducers or inhibitors of CYP2C9 and CYP3A4 in adult patients with chronic immune thrombocytopenia and pediatric patients 6 years and older with persistent or chronic immune thrombocytopenia are summarized in Table 4.

Table 4: DOPTELET Tablets Recommended Initial Dosage with Concomitant Moderate or Strong Dual Inducers or Inhibitors of CYP2C9 and CYP3A4 for Adult Patients with Chronic Immune Thrombocytopenia and Pediatric Patients 6 Years and Older with Persistent or Chronic Immune Thrombocytopenia

Concomitant Medications | Recommended Initial Dosage
Moderate or strong dual inhibitors of CYP2C9 and CYP3A4 | 20 mg (1 tablet) orally three times a week
Moderate or strong dual inducers of CYP2C9 and CYP3A4 | 40 mg (2 tablets) orally once daily

2.5 Recommended Dosage of DOPTELET SPRINKLE for Patients 1 Year to Less than 6 Years with Persistent or Chronic Immune Thrombocytopenia

Use the lowest dose of DOPTELET SPRINKLE needed to achieve and maintain a platelet count greater than or equal to 50×10^9/L as necessary to reduce the risk for bleeding. Dose adjustments are based on platelet count response. Do not use DOPTELET SPRINKLE to normalize platelet counts.

Initial Dosage:

- Begin DOPTELET SPRINKLE at an initial dosage of 10 mg (content of 1 capsule) orally once daily with food (see Table 6).
- The recommended initial dosages of DOPTELET SPRINKLE are different for patients receiving certain concomitant medications (see Table 7).

Monitoring:

After initiating therapy with DOPTELET SPRINKLE, assess platelet counts weekly until a stable platelet count greater than or equal to 50×10^9/L has been achieved, and then obtain platelet counts monthly thereafter. Obtain platelet counts weekly for at least 4 weeks following discontinuation of DOPTELET SPRINKLE.

Dose Adjustments:

DOPTELET SPRINKLE dose adjustments (see Table 5 and Table 6) are based on the platelet count response. Do not exceed a DOPTELET SPRINKLE daily dose of 20 mg (content of 2 capsules).

Table 5: DOPTELET SPRINKLE Dose Adjustments for Patients 1 Year to Less than 6 Years with Persistent or Chronic Immune Thrombocytopenia

Platelet Count | Dose Adjustment or Action
Less than 50×10^9/L after at least 2 weeks of DOPTELET SPRINKLE | - Increase One Dose Level per Table 6. - Wait 2 weeks to assess the effects of this regimen and any subsequent dose adjustments.
Between 200×10^9/L and 400×10^9/L | - Decrease One Dose Level per Table 6. - Wait 2 weeks to assess the effects of this regimen and any subsequent dose adjustments.
Greater than 400×10^9/L | - Stop DOPTELET SPRINKLE. - Increase platelet monitoring to twice weekly. - When platelet count is less than 150×10^9/L, decrease One Dose Level per Table 6 and reinitiate therapy.
Less than 50×10^9/L after 4 weeks of DOPTELET SPRINKLE 20 mg (content of 2 capsules) once daily | - Discontinue DOPTELET SPRINKLE.
Greater than 400×10^9/L after 2 weeks of DOPTELET SPRINKLE 10 mg (content of 1 capsule) weekly | - Discontinue DOPTELET SPRINKLE.

Table 6: DOPTELET SPRINKLE Dose Levels for Titration in Pediatric Patients 1 Year to Less than 6 Years with Persistent or Chronic Immune Thrombocytopenia

Dosage | Dose Level
20 mg (content of 2 capsules) orally Once Daily | 6
20 mg (content of 2 capsules) orally Three Times a Week AND 10 mg (content of 1 capsule) orally on the Four Remaining Days of Each Week | 5
10 mg (content of 1 capsule) orally Once Daily* | 4
10 mg (content of 1 capsule) orally Three Times a Week | 3
10 mg (content of 1 capsule) orally Twice a Week OR 20 mg (content of 2 capsules) orally Once Weekly | 2
10 mg (content of 1 capsule) orally Once Weekly | 1

*Initial dose regimen for all patients except those taking Moderate or Strong Dual Inducers or Moderate or Strong Dual Inhibitors of CYP2C9 and CYP3A4.

Discontinuation:

- Discontinue DOPTELET SPRINKLE if the platelet count does not increase to greater than or equal to 50×10^9/L after 4 weeks of dosing at the maximum dose of 20 mg (content of 2 capsules) once daily.
- Discontinue DOPTELET SPRINKLE if the platelet count is greater than 400×10^9/L after 2 weeks of dosing at 10 mg (content of 1 capsule) once weekly.

2.6 Recommended Initial Dosage of DOPTELET SPRINKLE with Concomitant Moderate or Strong Dual Inducers or Inhibitors of CYP2C9 and CYP3A4

The recommended initial dosages of DOPTELET SPRINKLE with concomitant moderate or strong dual inducers or inhibitors of CYP2C9 and CYP3A4 in pediatric patients 1 year to less than 6 years with persistent or chronic immune thrombocytopenia are summarized in Table 7.

Table 7: DOPTELET SPRINKLE Recommended Initial Dosage with Concomitant Moderate or Strong Dual Inducers or Inhibitors of CYP2C9 and CYP3A4 for Pediatric Patients 1 Year to Less than 6 Years with Persistent or Chronic Immune Thrombocytopenia

Concomitant Medications | Recommended Initial Dosage
Moderate or strong dual inhibitors of CYP2C9 and CYP3A4 | 10 mg (content of 1 capsule) orally three times a week
Moderate or strong dual inducers of CYP2C9 and CYP3A4 | 20 mg (content of 2 capsules) orally once daily

2.7 Important Preparation and Administration Instructions for DOPTELET SPRINKLE

- Open the capsules and sprinkle the granules onto a small amount of a soft food or liquid in a spoon or cup.
- Do not swallow the capsules whole. Do not chew or crush the granules.
- Use the entire contents of the capsules to achieve the dose.
  - The following soft foods and liquids are suitable:
    - Soft foods: applesauce; strawberry jelly; yogurt (plain)
    - Liquids: milk (whole or skim); orange juice; pediatric electrolyte solution (unflavored); water
- Mix the granules into the soft food or liquid; the granules will not dissolve.
- Consume the mixture immediately after preparation; it should not be saved for future use.
- Rinse the spoon or cup with the soft food or liquid to ensure that the full dose is administered.

2.8 Missed Dose

In the case of a missed dose of DOPTELET tablets or DOPTELET SPRINKLE, patients should take the missed dose as soon as they remember. Patients should not take two doses at one time to make up for a missed dose and should take the next dose at the usual time the next day.

3 DOSAGE FORMS AND STRENGTHS

Tablets

DOPTELET Tablets: 20 mg as round, biconvex, yellow, film-coated tablets debossed with “AVA” on one side and “20” on the other side.

Oral Granules

DOPTELET SPRINKLE: 10 mg as Size 0 capsules containing white to off-white granules. The capsules have a white opaque body and light blue opaque cap with a black arrow symbol imprinted on the body and cap.

4 CONTRAINDICATIONS

None.

5 WARNINGS AND PRECAUTIONS

5.1 Thrombotic/Thromboembolic Complications

DOPTELET is a thrombopoietin (TPO) receptor agonist and TPO receptor agonists have been associated with thrombotic and thromboembolic complications in patients with chronic liver disease or immune thrombocytopenia. In patients with chronic liver disease, thromboembolic events (portal vein thrombosis) occurred in 0.4% (1/274) of patients receiving DOPTELET. In adult patients with chronic immune thrombocytopenia, thromboembolic events (arterial or venous) occurred in 7% (9/128) of patients receiving DOPTELET.

Consider the potential increased thrombotic risk when administering DOPTELET to patients with known risk factors for thromboembolism, including genetic prothrombotic conditions (e.g., Factor V Leiden, Prothrombin 20210A, Antithrombin deficiency or Protein C or S deficiency) and acquired risk factors (e.g., antiphospholipid syndrome).

DOPTELET should not be administered to patients with chronic liver disease or immune thrombocytopenia in an attempt to normalize platelet counts. Monitor platelet counts and follow the dosing guidelines to achieve target platelet counts [see Dosage and Administration (2.3 and 2.5)]. Monitor patients receiving DOPTELET for signs and symptoms of thromboembolic events and institute treatment promptly.

6 ADVERSE REACTIONS

The following clinically significant adverse reactions are discussed in detail in other sections of the labeling:

- Thrombotic/Thromboembolic Complications [see Warnings and Precautions (5.1)]

6.1 Clinical Trial Experience

Because clinical trials are conducted under widely varying conditions, adverse reaction rates observed in the clinical trials of a drug cannot be directly compared to rates in the clinical trials of another drug and may not reflect the rates observed in practice.

Patients with Chronic Liver Disease

The safety of DOPTELET was evaluated in two international, identically designed, randomized, double-blind, placebo-controlled trials, ADAPT-1 and ADAPT-2, in which 430 patients with chronic liver disease and thrombocytopenia received either DOPTELET (n=274) or placebo (n=156) daily for 5 days prior to a scheduled procedure, and had 1 post-dose safety assessment. Patients were divided into two groups based on their mean platelet count at baseline:

- Low Baseline Platelet Count Cohort (less than 40×10^9/L) who received DOPTELET 60 mg once daily for 5 days
- High Baseline Platelet Count Cohort (40 to less than 50×10^9/L) who received DOPTELET 40 mg once daily for 5 days

The majority of patients were males (65%) and median subject age was 58 years (ranging from 19-86 years of age). The racial and ethnic distribution was White (60%), Asian (33%), Black (3%) and Other (3%).

The most common adverse reactions (those occurring in ≥3% of patients) in the DOPTELET-treated groups (60 mg or 40 mg) across the pooled data from the two trials are summarized in Table 8.

Table 8: Adverse Reactions with a Frequency ≥3% in Patients with Chronic Liver Disease Treated with DOPTELET – Pooled Data ADAPT-1 and ADAPT-2

Adverse Reactions | Low Baseline Platelet Count Cohort (˂40×10^9/L) |  | High Baseline Platelet Count Cohort (≥40 to ˂50×10^9/L) |  | Combined Baseline Platelet Count Cohorts (˂50×10^9/L)
 | DOPTELET 60 mg (N=159) % | Placebo (N=91) % | DOPTELET 40 mg (N=115) % | Placebo (N=65) % | Total DOPTELET (N=274) % | Total Placebo (N=156) %
Pyrexia | 11 | 9 | 8 | 9 | 10 | 9
Abdominal Pain | 6 | 7 | 7 | 6 | 7 | 6
Nausea | 6 | 8 | 7 | 6 | 7 | 7
Headache | 4 | 8 | 7 | 5 | 6 | 6
Fatigue | 4 | 4 | 3 | 2 | 4 | 3
Edema Peripheral | 3 | 2 | 4 | 2 | 3 | 2

For the Low Baseline Platelet Count Cohort, the incidence of serious adverse reactions was 7% (11/159) in the 60 mg DOPTELET treatment group. For the High Baseline Platelet Count Cohort, the incidence of serious adverse reactions was 8% (9/115) in the 40 mg DOPTELET treatment group. The most common serious adverse reaction reported with DOPTELET was hyponatremia. Two DOPTELET-treated patients (0.7%) developed hyponatremia.

Adverse reactions resulting in discontinuation of DOPTELET were anemia, pyrexia, and myalgia; each was reported in a single (0.4%) patient in the DOPTELET (60 mg) treatment group.

Adult Patients with Chronic Immune Thrombocytopenia

The safety of DOPTELET was evaluated in four clinical trials in adult patients with chronic immune thrombocytopenia: two Phase 3 trials (one randomized, double-blind, placebo-controlled trial, and one randomized, double-blind, active-controlled trial) and two Phase 2 trials (one randomized, double-blind, placebo-controlled, dose-ranging, trial, and one open-label extension trial) in 161 patients with chronic immune thrombocytopenia in both the double-blind and open-label extension phases.

The pooled safety data from these four clinical trials includes 128 patients who received 2.5 to 40 mg of DOPTELET once daily for a median duration of exposure of 29.1 weeks and had 1 post-dose safety assessment. The majority of patients were female (63%) and median subject age was 50.5 years (ranging from 18-88 years of age). The racial and ethnic distribution was White (84%), Black (6%), Asian (6%) and Other (6%).

The most common adverse reactions (those occurring in ≥10% of patients) in the DOPTELET-treated patients across the pooled safety data from the four trials are summarized in Table 9.

Table 9: Adverse Reactions with a Frequency ≥10% in Adult Patients with Chronic Immune Thrombocytopenia Treated with DOPTELET – Pooled Data from Clinical Trials

Adverse Reactions | DOPTELET; (N=128); % | Placebo; (N= 22); %
Headache | 31 | 14
Fatigue | 28 | 9
Contusion | 26 | 18
Epistaxis | 19 | 18
Upper Respiratory Tract Infection | 15 | 5
Arthralgia | 13 | 0
Gingival Bleeding | 13 | 0
Petechiae | 11 | 9
Nasopharyngitis | 10 | 0

The incidence of serious adverse reactions was 9% (12/128) in the DOPTELET treatment group. Serious adverse reactions reported in more than 1 individual DOPTELET-treated patient included headache, occurring in 1.6% (2/128).

Adverse reactions resulting in discontinuation of DOPTELET that were reported in more than 1 patient included headache, occurring in 1.6% (2/128).

Pediatric Patients with Persistent or Chronic Immune Thrombocytopenia

The data described below reflect median exposure to DOPTELET of 12 weeks for 54 pediatric patients (≥1 to <18 years of age) with persistent or chronic immune thrombocytopenia across the core phase of one double-blind, placebo-controlled trial [see Clinical Studies (14.3)].

Table 10 presents the most common adverse reactions (experienced by greater than or equal to 10% of pediatric patients 1 year and older receiving DOPTELET) with a higher incidence for DOPTELET versus placebo.

Table 10: Adverse Reactions in Pediatric Patients with Persistent or Chronic Immune Thrombocytopenia Treated with DOPTELETa

Adverse Reactions | DOPTELET(N=54) % | Placebo(N=21) %
Viral Infectionb | 20 | 5
Nasopharyngitis | 20 | 10
Cough | 17 | 0
Pyrexia | 17 | 0
Oropharyngeal Pain | 13 | 0

a Adverse reactions that occurred in ≥10% of DOPTELET-treated patients and ≥2% more than placebo-treated patients.

b Viral infection includes viral upper respiratory infection, viral infection, COVID-19, parainfluenza virus infection, and rhinovirus infection.

Two patients experienced serious adverse reactions: thrombocytosis and headache. Two patients experienced adverse reactions resulting in discontinuation of DOPTELET: vomiting and headache (in one patient) and leukocytosis (in one patient).

6.2 Postmarketing Experience

The following adverse reactions have been identified during post approval use of DOPTELET. Because these reactions are reported voluntarily from a population of uncertain size, it is not always possible to reliably estimate their frequency or establish a causal relationship to drug exposure.

Immune System Disorders: Hypersensitivity reactions including pruritus, rash, choking sensation, erythema, pharyngeal edema, pruritus generalized, rash macular, swelling face, and swollen tongue.

7 DRUG INTERACTIONS

7.1 Effect of Other Drugs on DOPTELET in Patients with Persistent or Chronic Immune Thrombocytopenia

Moderate or Strong Dual Inhibitors of CYP2C9 and CYP3A4

Concomitant use with a moderate or strong dual inhibitor of CYP2C9 and CYP3A4 increases avatrombopag AUC [see Clinical Pharmacology (12.3)], which may increase the risk of DOPTELET toxicities. Reduce the starting dosage of DOPTELET when used concomitantly with a moderate or strong dual inhibitor of CYP2C9 and CYP3A4 (see Table 4 and Table 7) [see Dosage and Administration (2.4 and 2.6)].

In patients starting moderate or strong dual inhibitors of CYP2C9 and CYP3A4 while receiving DOPTELET, monitor platelet counts and adjust DOPTELET dose as necessary (see Table 2 and Table 3; and Table 5 and Table 6) [see Dosage and Administration (2.3 and 2.5)].

Moderate or Strong Dual Inducers of CYP2C9 and CYP3A4

Concomitant use with a moderate or strong dual inducer of CYP2C9 and CYP3A4 decreases avatrombopag AUC [see Clinical Pharmacology (12.3)], which may reduce DOPTELET efficacy. Increase the recommended starting dosage of DOPTELET when used concomitantly with a moderate or strong dual inducer of CYP2C9 and CYP3A4 (see Table 4 and Table 7) [see Dosage and Administration (2.4 and 2.6)].

In patients starting moderate or strong dual inducers of CYP2C9 and CYP3A4 while receiving DOPTELET, monitor platelet counts and adjust DOPTELET dose as necessary (see Table 2 and Table 3; and Table 5 and Table 6) [see Dosage and Administration (2.3 and 2.5)].

Patients with Chronic Liver Disease

No dosage adjustments are required for patients with chronic liver disease.

8 USE IN SPECIFIC POPULATIONS

8.1 Pregnancy

Risk Summary

Based on findings from animal reproduction studies, DOPTELET may cause fetal harm when administered to a pregnant woman (see Data). The available data on DOPTELET in pregnant women are insufficient to inform a drug-associated risk of adverse developmental outcomes. In animal reproduction studies, oral administration of avatrombopag resulted in adverse developmental outcomes when administered during organogenesis in rabbits and during organogenesis and the lactation period in rats. However, these findings were observed at exposures based on an AUC substantially higher than the AUC observed in patients at the maximum recommended dose of 60 mg once daily. Advise pregnant women of the potential risk to a fetus.

The estimated background risk of major birth defects and miscarriage for the indicated population is unknown. All pregnancies have a background risk of birth defect, loss, or other adverse outcomes. In the U.S. general population, the estimated background risk of major birth defects and of miscarriage in clinically recognized pregnancies is 2-4% and 15-20%, respectively.

Data

Animal Data

In embryo-fetal development studies, avatrombopag was administered during organogenesis at doses of 100, 300, and 1000 mg/kg/day in rats and doses of 100, 300, and 600 mg/kg/day in rabbits. Minimal decreases in fetal weights were observed in rats at the maternally toxic dose of 1000 mg/kg/day with exposures 190 times the human exposure based on AUC. Spontaneous abortions were observed at all doses tested in rabbits and were associated with decreased body weights and food consumption at 300 and 600 mg/kg/day; exposures at the lowest dose of 100 mg/kg/day were 10 times the AUC in patients at the maximum recommended dose of 60 mg once daily. There were no embryo-fetal effects in rats administered avatrombopag at doses up to 100 mg/kg/day (53 times the human exposure based on AUC) or rabbits administered avatrombopag at doses up to 600 mg/kg (35 times the human exposure based on AUC).

In pre- and postnatal development studies in rats, avatrombopag was administered during both the organogenesis and lactation periods at doses ranging from 5 to 600 mg/kg/day. Doses of 100, 300, and 600 mg/kg/day caused maternal toxicity leading to total litter losses, decreased body weight in pups, and increased pup mortality, with the majority of the pup mortality occurring from postnatal days 14 to 21. At a dose of 50 mg/kg/day that did not produce clear maternal toxicity, avatrombopag caused increased pup mortality from postnatal days 4 to 21, and mortality continued through postnatal day 25. The 50 mg/kg/day dose also decreased body weight gain in the pups, resulting in a delay in sexual maturation. There were no effects on behavioral or reproductive functions in the offspring. The 50 mg/kg/day dose resulted in maternal exposures 43 times and pup exposures approximately 3 times the AUC observed in patients at the maximum recommended dose of 60 mg once daily.

8.2 Lactation

Risk Summary

There is no information regarding the presence of avatrombopag in human milk, the effects on the breastfed child, or the effects on milk production. Avatrombopag was present in the milk of lactating rats. When a drug is present in animal milk, it is likely the drug will be present in human milk. Due to the potential for serious adverse reactions in a breastfed child from DOPTELET, breastfeeding is not recommended during treatment with DOPTELET and for at least 2 weeks after the last dose (see Clinical Considerations).

Clinical Considerations

Minimizing Exposure

A lactating woman receiving DOPTELET for brief periods, such as prior to an invasive procedure, should interrupt breastfeeding and pump and discard breastmilk during treatment and for two weeks after the last dose of DOPTELET in order to minimize exposure to a breastfed child. Advise lactating women receiving chronic DOPTELET therapy not to breastfeed during treatment with DOPTELET and for at least 2 weeks after the last dose.

8.4 Pediatric Use

The safety and effectiveness of DOPTELET tablet for the treatment of persistent or chronic ITP have been established in pediatric patients aged 6 years and older. The safety and effectiveness of DOPTELET SPRINKLE for the treatment of persistent or chronic ITP have been established in pediatric patients aged 1 to <6 years. Use of DOPTELET tablet and DOPTELET SPRINKLE for their respective populations is supported by evidence from an adequate and well-controlled study in pediatric patients aged 1 year and older [see Adverse Reactions (6.1), Clinical Pharmacology (12.3), and Clinical Studies (14.3)].

Juvenile Animal Toxicity Data

In a 10-week juvenile toxicology study in rats, avatrombopag was administered at doses ranging from 20 to 300 mg/kg/day. There was no test article-related mortality and there were no clinical signs at doses up to 300 mg/kg/day. In the stomach, dose-dependent degeneration, regenerative hyperplasia, and atrophy of the glandular epithelium occurred at 100 and 300 mg/kg/day; exposures at 100 mg/kg/day in male rats were 14 times the AUC in patients at the highest recommended dose of 60 mg once daily. An increased incidence of background focal mineralization was also observed in the kidneys of females at 300 mg/kg/day (female rat exposure was 50 times the human exposure based on AUC at the 60 mg daily dose).

8.5 Geriatric Use

There were 112 patients 65 years of age and older in the clinical studies for Chronic Liver Disease and Chronic Immune Thrombocytopenia [see Clinical Studies (14.1 and 14.2)]. Of the total number of DOPTELET-treated patients in these studies, 71 (23%) were 65 years of age and older, while 12 (4%) were 75 years of age and older. Clinical studies of DOPTELET did not include sufficient numbers of subjects aged 65 and over to determine whether they respond differently from younger subjects. Other reported clinical experience has not identified differences in responses between the elderly and younger patients.

10 OVERDOSAGE

In the event of overdose, platelet count may increase excessively and result in thrombotic or thromboembolic complications. Closely monitor the patient and platelet count. Treat thrombotic complications in accordance with standard of care.

No antidote for DOPTELET overdose is known.

Hemodialysis is not expected to enhance the elimination of DOPTELET because avatrombopag is only approximately 6% renally excreted and is highly bound to plasma proteins.

Consider contacting the Poison Help line (1-800-222-1222) or a medical toxicologist for additional overdose management recommendations.

11 DESCRIPTION

The active ingredient in DOPTELET is avatrombopag maleate, a thrombopoietin receptor agonist. The chemical name of avatrombopag maleate is 4-piperidinecarboxylic acid, 1-[3-chloro-5-[[[4-(4-chloro-2-thienyl)-5-(4-cyclohexyl-1-piperazinyl)-2-thiazolyl]amino]carbonyl]-2-pyridinyl]-, (2Z)-2-butenedioate (1:1). It has the molecular formula C29H34Cl2N6O3S2 · C4H4O4. The molecular weight is 765.73.

The structural formula is:

The aqueous solubility of avatrombopag maleate at various pH levels indicates that the drug substance is practically insoluble at pH 1 to 11.

DOPTELET is provided as an immediate-release tablet and as a sprinkle capsule that contains oral granules.

Each DOPTELET tablet contains 20 mg avatrombopag (equivalent to 23.6 mg of avatrombopag maleate) and the following inactive ingredients: colloidal silicon dioxide, crospovidone, lactose monohydrate, magnesium stearate, and microcrystalline cellulose. Coating film: ferric oxide yellow, polyethylene glycol, polyvinyl alcohol, talc, and titanium dioxide.

Each DOPTELET SPRINKLE capsule contains 10 mg avatrombopag (equivalent to 11.8 mg of avatrombopag maleate) and the following inactive ingredients: crospovidone Type A, magnesium stearate, mannitol, microcrystalline cellulose, and sodium lauryl sulfate. Capsule shells: Hypromellose.

12 CLINICAL PHARMACOLOGY

12.1 Mechanism of Action

Avatrombopag is an orally bioavailable, small molecule TPO receptor agonist that stimulates proliferation and differentiation of megakaryocytes from bone marrow progenitor cells, resulting in an increased production of platelets. Avatrombopag does not compete with TPO for binding to the TPO receptor and has an additive effect with TPO on platelet production.

12.2 Pharmacodynamics

Platelet Response

DOPTELET tablet administered to adult patients resulted in dose- and exposure-dependent elevations in platelet counts. The onset of the platelet count increase was observed within 3 to 5 days of the start of treatment, with peak effect after 10 to 13 days. Post treatment, platelet counts decreased gradually, returning to near baseline values.

Cardiac Electrophysiology

At exposures similar to that achieved at the 40 mg and 60 mg tablet dose, DOPTELET did not prolong the QT interval to any clinically relevant extent. Mean QTc prolongation effects >20 ms are not anticipated with the highest recommended therapeutic dosing regimen based on analysis of data from the pooled clinical trials in patients with chronic liver disease.

12.3 Pharmacokinetics

The pharmacokinetics of avatrombopag were determined following administration of DOPTELET tablets, and pharmacokinetic parameters are presented as geometric mean (CV%) unless otherwise specified. Avatrombopag demonstrated dose-proportional pharmacokinetics after single doses from 10 mg (0.5 times the lowest approved dosage) to 80 mg (1.3 times the highest recommended dosage). Healthy subjects administered 40 mg of avatrombopag had a geometric mean (%CV) maximal concentration (Cmax) of 166 (84%) ng/mL and area under the time-concentration curve extrapolated to infinity (AUC0-inf) of 4198 (83%) ng.hr/mL. The pharmacokinetics of avatrombopag were similar in both healthy subjects and the chronic liver disease population.

The relative bioavailability of DOPTELET SPRINKLE compared to DOPTELET tablet has not been studied. However, a prototype of DOPTELET SPRINKLE demonstrated a 22% higher geometric mean Cmax and a 38% higher geometric mean AUC for avatrombopag compared to DOPTELET tablet, both administered to healthy adult subjects under the fed condition.

Table 11 summarizes avatrombopag exposure in a virtual adult population and in pediatric patients with persistent or chronic immune thrombocytopenia.

Table 11: Summary of Avatrombopag Exposure in a Virtual Adult Population and Pediatric Patients with Persistent or Chronic Immune Thrombocytopenia

Cohort | Adults; 20 mg daily DOPTELET tablet | ≥12 to <18 years; N=21; 20 mg daily DOPTELET tablet | ≥6 to <12 years; N=20; 20 mg daily DOPTELET tablet | ≥1 to <6 years; N=12; 10 mg daily DOPTELET SPRINKLE
Cmax,ss (ng/mL)
Geometric mean (CV) | 165 (61.3) | 168 (36.7) | 267 (25.7) | 221 (35.6)
AUCss (ng × h/mL)
Geometric mean (CV) | 3277 (62.2) | 3372 (41.5) | 4942 (28.7) | 4030 (38.6)

AUCss = area under the concentration time curve at steady-state; Cmax,ss = maximal concentration at steady-state;
CV = coefficient of variation expressed as a percent; N = number of individuals.

Absorption

The median time to maximal concentration (Tmax) occurred at 5 to 6 hours post-dose.

Effect of Food

Avatrombopag AUC0-inf and Cmax were not affected when DOPTELET tablets were co-administered with a low-fat meal (500 calories, 3 g fat, 15 g protein, and 108 g carbohydrates) or a high-fat meal (918 calories, 59 g fat, 39 g protein, and 59 g carbohydrates). The variability of avatrombopag exposure was reduced by 40% to 60% with food. The Tmax of avatrombopag was delayed by 0 to 2 hours when DOPTELET tablets were administered with a low-fat or high-fat meal (median Tmax range 5 to 8 hours) compared to the fasted state.

Geometric mean exposure increased by approximately 19% and 32% for Cmax and AUC, respectively, when a prototype of DOPTELET SPRINKLE was administered in the fed state compared to the fasted state, and between-subject variability estimates for AUC and Cmax were decreased after administration in the fed state.

Distribution

Avatrombopag has an estimated mean apparent volume of distribution (%CV) of 180 L (25%). Avatrombopag is greater than 96% bound to human plasma proteins.

Elimination

The mean plasma elimination half-life (%CV) of avatrombopag is approximately 19 hours (19%). The mean (%CV) of the apparent clearance of avatrombopag is estimated to be 6.9 L/hr (29%).

Metabolism

Avatrombopag is primarily metabolized by cytochrome P450 CYP2C9 and CYP3A4.

Excretion

Fecal excretion accounted for 88% of the administered dose, with 34% of the dose excreted as unchanged avatrombopag. Only 6% of the administered dose was found in urine.

Specific Populations

Age (1-86 years), sex, race [Whites, African-Americans, and East Asians (i.e., Japanese, Chinese and Koreans)], and any hepatic impairment (Child-Turcotte-Pugh (CTP) grade A, B, and C, or Model for End-Stage Liver Disease (MELD) score 4-23) and mild to moderate renal impairment (CLcr ≥30 mL/min) did not have clinically meaningful effects on the pharmacokinetics of avatrombopag.

Lower body weight was associated with higher avatrombopag Cmax and AUC following the proposed starting dose in patients aged 6 years and older weighing 16.3 to 175 kg. Pediatric patients aged 1 to less than 6 years had 34% higher Cmax and 23% higher AUC following administration of 10 mg daily DOPTELET SPRINKLE compared to adults who received 20 mg daily DOPTELET tablets.

The effect of severe renal impairment (CLcr <30 mL/min, Cockcroft-Gault), including patients requiring hemodialysis, on avatrombopag pharmacokinetics is unknown.

Drug Interactions

Clinical Studies

Table 12 summarizes the effect of other drugs on the pharmacokinetics of avatrombopag.

Table 12: Drug Interactions: Changes in Pharmacokinetics of Avatrombopag in the Presence of Co-Administered Drug

Co-administered Drug* | Geometric Mean Ratio (90% CI) of Avatrombopag PK with/without Co-administered Drug [No Effect=1.00]
Co-administered Drug* | AUC0-inf | Cmax
Strong CYP3A Inhibitor
Itraconazole | 1.37 (1.10, 1.72) | 1.07 (0.86, 1.35)
Moderate CYP3A and CYP2C9 Inhibitor
Fluconazole | 2.16 (1.71, 2.72) | 1.17 (0.96, 1.42)
Moderate CYP2C9 and Strong CYP3A Inducer
Rifampin | 0.57 (0.47, 0.62) | 1.04 (0.88, 1.23)
P-gp Inhibitor
Cyclosporine | 0.83 (0.65, 1.04) | 0.66 (0.54, 0.82)
P-gp and Moderate CYP3A Inhibitor
Verapamil | 1.61 (1.21, 2.15) | 1.26 (0.96, 1.66)

*at steady state, except for cyclosporine which was administered as a single dose.

In Vitro Studies Where Drug Interaction Potential Was Not Further Evaluated Clinically

CYP enzymes: Avatrombopag does not inhibit CYP1A, CYP2B6, CYP2C8, CYP2C9, CYP2C19, CYP2D6, CYP2E1 or CYP3A, does not induce CYP1A, CYP2B6, CYP2C or CYP3A, and weakly induces CYP2C8 and CYP2C9.

Transporter systems: Avatrombopag inhibits organic anion transporter (OAT) 3 and breast cancer resistance protein (BCRP), but not organic anion transporter polypeptide (OATP) 1B1 or 1B3, organic cation transporter (OCT) 2 or OAT1.

Avatrombopag is not a substrate for OATP1B1, OATP1B3, OCT2, OAT1 or OAT3.

12.5 Pharmacogenomics

The CYP2C9*2 and CYP2C9*3 loss-of-function polymorphisms result in reduced CYP2C9 enzymatic activity. In a pooled pharmacogenomic analysis of avatrombopag studies, subjects heterozygous for CYP2C9 loss-of-function polymorphisms (intermediate metabolizers [n=24]) had approximately 1.4-fold higher exposure and subjects homozygous for CYP2C9 loss-of-function polymorphisms (poor metabolizers [n=2]) had approximately 2-fold higher exposure compared to subjects wild-type for CYP2C9 (normal metabolizers [n=94]).

13 NONCLINICAL TOXICOLOGY

13.1 Carcinogenesis, Mutagenesis, Impairment of Fertility

In two-year carcinogenicity studies, avatrombopag was administered orally at doses of 20, 60, and 160 mg/kg/day in mice and doses of 20, 50, and 160 mg/kg/day in rats. Avatrombopag induced a statistically significant increase in neuroendocrine cell (enterochromaffin-like cell, ECL cell) gastric tumors (carcinoids) in the stomach at 160 mg/kg in female rats. The 160 mg/kg/day dose resulted in exposures 117 times the AUC observed in patients at the maximum recommended dose of 60 mg once daily. The gastric carcinoids were considered likely due to prolonged hypergastrinemia observed in toxicity studies. Hypergastrinemia-related gastric carcinoids in rodents are generally considered to be of low risk or relevance to humans.

Avatrombopag was not mutagenic in an in vitro bacterial reverse mutation (Ames) assay or clastogenic in an in vitro human lymphocyte chromosomal aberrations assay or in an in vivo rat bone marrow micronucleus assay.

Avatrombopag did not affect fertility or early embryonic development in male rats at exposures 22 times, or in female rats at exposures 114 times, the AUC observed in patients at the maximum recommended dose of 60 mg once daily.

14 CLINICAL STUDIES

14.1 Patients with Chronic Liver Disease

The efficacy of DOPTELET for the treatment of thrombocytopenia in patients with chronic liver disease who are scheduled to undergo a procedure was established in 2 identically-designed multicenter, randomized, double-blind, placebo-controlled trials (ADAPT-1 [NCT01972529] and ADAPT-2 [NCT01976104]). In each trial, patients were assigned to the Low Baseline Platelet Count Cohort (<40×10] and ADAPT-2 [NCT01976104]). In each trial, patients were assigned to the Low Baseline Platelet Count Cohort (<40×10^9/L) or the High Baseline Platelet Count Cohort (≥40 to <50×10^9/L) based on their platelet count at baseline. Patients were then randomized in a 2:1 ratio to either DOPTELET or placebo. Patients were stratified according to hepatocellular cancer (HCC) status and risk of bleeding associated with the elective procedure (low, moderate, or high). Patients undergoing neurosurgical interventions, thoracotomy, laparotomy or organ resection were not eligible for enrollment.

Patients in the Low Baseline Platelet Count Cohort received 60 mg DOPTELET or matching placebo once daily for 5 days, and patients in the High Baseline Platelet Count Cohort received 40 mg DOPTELET or matching placebo once daily for 5 days. Eligible patients were scheduled to undergo their procedure (low, moderate, or high bleeding risk) 5 to 8 days after their last dose of treatment. Patient populations were similar between the pooled Low and High Baseline Platelet Count Cohorts and consisted of 66% male and 35% female; median age 58 years and 61% White, 34% Asian, and 3% Black.

In ADAPT-1, a total of 231 patients were randomized, 149 patients were treated with DOPTELET and 82 patients were treated with placebo. In the Low Baseline Platelet Count Cohort, the mean baseline platelet count for the DOPTELET-treated group was 31.1×10^9/L and for the placebo-treated patients was 30.7×10^9/L. In the High Baseline Platelet Count Cohort, the mean baseline platelet count for the DOPTELET-treated patients was 44.3×10^9/L and for placebo-treated patients was 44.9×10^9/L.

In ADAPT-2, a total of 204 patients were randomized, 128 patients were treated with DOPTELET and 76 patients were treated with placebo. In the Low Baseline Platelet Count Cohort, the mean baseline platelet count for the DOPTELET-treated group was 32.7×10^9/L and for the placebo-treated patients was 32.5×10^9/L. In the High Baseline Platelet Count Cohort, the mean baseline platelet count for the DOPTELET-treated patients was 44.3×10^9/L and for the placebo-treated patients was 44.5×10^9/L.

Across both baseline platelet count cohorts and the avatrombopag and placebo treatment groups, patients underwent a broad spectrum of types of scheduled procedures that ranged from low to high bleeding risk. Overall, the majority of patients (60.8% [248/430] subjects) in all treatment groups underwent low bleeding risk procedures, 17.2% (70/430) of patients underwent procedures associated with moderate bleeding risk, and 22.1% (90/430) of subjects underwent procedures associated with high bleeding risk. The proportions of patients undergoing low, moderate, and high-risk procedures were similar between the avatrombopag and placebo treatment groups.

The major efficacy outcome was the proportion of patients who did not require a platelet transfusion or any rescue procedure for bleeding after randomization and up to 7 days following an elective procedure. Additional secondary efficacy outcomes were the proportion of patients who achieved platelet counts of >50×10^9/L on the day of procedure, and the change in platelet count from baseline to procedure day.

Responders were defined as patients who did not require a platelet transfusion or any rescue procedure for bleeding after randomization and up to 7 days following a scheduled procedure. The following were considered rescue therapies to manage the risk of bleeding associated with a procedure: whole blood transfusion, packed red blood cell (RBC) transfusion, platelet transfusion, fresh frozen plasma (FFP) or cryoprecipitate administration, Vitamin K, desmopressin, recombinant activated factor VII, aminocaproic acid, tranexamic acid, or surgical or interventional radiology procedures performed to achieve hemostasis and control blood loss. In both baseline platelet count cohorts, patients in the DOPTELET treatment groups had a greater proportion of responders than the corresponding placebo treatment groups that was both clinically meaningful and statistically significant as detailed in Table 13.

Table 13: Proportion of Patients Not Requiring a Platelet Transfusion or Any Rescue Procedure for Bleeding by Baseline Platelet Count Cohort and Treatment Group – ADAPT-1 and ADAPT-2

Low Baseline Platelet Count Cohort (<40×10^9/L)
Category | ADAPT-1 |  | ADAPT-2
 | DOPTELET 60 mg (n=90) | Placebo (n=48) | DOPTELET 60 mg (n=70) | Placebo (n=43)
Responders 95% CIa | 66% (56, 75) | 23% (11, 35) | 69% (58, 79) | 35% (21, 49)
Difference of Proportion vs. Placebob 95% CIc | 43% (27, 58) |  | 34% (16, 52)
p-valued | ˂0.0001 |  | 0.0006
High Baseline Platelet Count Cohort (≥40 to <50×10^9/L)
Category | ADAPT-1 |  | ADAPT-2
 | DOPTELET 40 mg (n=59) | Placebo (n= 34) | DOPTELET 40 mg (n=58) | Placebo (n=33)
Responders 95% CIa | 88% (80, 96) | 38% (22, 55) | 88% (80, 96) | 33% (17, 49)
Difference of Proportion vs. Placebob 95% CIc | 50% (32, 68) |  | 55% (37, 73)
p-valued | ˂0.0001 |  | ˂0.0001

1. Two-sided 95% confidence interval based on normal approximation.
2. Difference of Proportion vs. placebo = Proportion of Responders for DOPTELET – Proportion of Responders for placebo.
3. 95% confidence interval calculated based on normal approximation.
4. By Cohhran-Mantel-Haenszel Testing stratified by bleeding risk for the procedure.

In addition, both trials demonstrated a higher proportion of patients who achieved the target platelet count of ≥50×10^9/L on the day of procedure, a secondary efficacy endpoint, in both DOPTELET-treated groups versus the placebo-treated groups for both cohorts (Low Baseline Platelet Count Cohort – ADAPT-1: 69% vs 4%, respectively; p˂0.0001, ADAPT-2: 67% vs 7%, respectively; p <0.0001; High Baseline Platelet Count Cohort – ADAPT-1: 88% vs 21%, respectively; p <0.0001: ADAPT-2: 93% vs 39%, respectively; p <0.0001). Further, both trials demonstrated a greater mean change in platelet counts from baseline to the day of the procedure, a secondary efficacy endpoint, in both DOPTELET-treated groups versus the placebo-treated groups for both cohorts (Low Baseline Platelet Count Cohort – ADAPT-1: 32×10^9/L vs 0.8×10^9/L, respectively; p<0.0001; ADAPT-2: 31.3×10^9/L vs 3.0×10^9/L, respectively; p <0.0001; High Baseline Platelet Count Cohort – ADAPT-1: 37.1×10^9/L vs 1.0×10^9/L, respectively; p <0.0001; ADAPT-2: 44.9×10^9/L vs 5.9×10^9/L, respectively; p <0.0001).

A measured increase in platelet counts was observed in both DOPTELET treatment groups over time beginning on Day 4 post-dose, that peaked on Day 10-13, decreased 7 days post-procedure, and then returned to near baseline values by Day 35.

14.2 Adult Patients with Chronic Immune Thrombocytopenia

Randomized Phase 3 Clinical Trial

The efficacy of DOPTELET in adult patients with chronic immune thrombocytopenia was evaluated in a Phase 3, multicenter, randomized, double-blind, placebo-controlled trial (NCT01438840). Patients had previously received one or more prior chronic immune thrombocytopenia therapies and had an average of screening and baseline platelet counts <30×10^9/L. Patients were centrally stratified by splenectomy status, baseline platelet count (≤15×10^9/L or >15×10^9/L to <30×10^9/L), and use of concomitant chronic immune thrombocytopenia medication, and then randomized (2:1) to receive either DOPTELET or placebo for 6 months. Patients received a starting dose of 20 mg once daily, with doses subsequently titrated based on platelet response.

Forty-nine patients were randomized, 32 to DOPTELET and 17 to placebo, with similar mean [SD] baseline platelet counts in the 2 treatment groups (14.1 [8.6]×10^9/L and 12.7 [7.8]×10^9/L, respectively). The median age was 44 years, 63% were female, and 94% were Caucasian, 4% Asian and 2% Black. The median duration of exposure was 26 weeks for DOPTELET-treated patients and 6 weeks for placebo-treated patients. The major efficacy outcome in this trial was the cumulative number of weeks in which the platelet count was ≥50×10^9/L during the 6-month treatment period in the absence of rescue therapy. DOPTELET-treated patients had a longer duration of platelet counts ≥50×10^9/L in the absence of rescue therapy than those who received placebo (median 12.4 [0, 25] vs 0 [0, 2] weeks, respectively, p<0.0001) (see Table 14).

Table 14: Cumulative Number of Weeks of Platelet Response–Phase 3 Trial in Adult Patients with Chronic Immune Thrombocytopenia

Primary Efficacy Analysis | DOPTELET (n=32) | Placebo (n=17)
Cumulative Number of Weeks with a Platelet Response*
Mean (SD) | 12.0 (8.75) | 0.1 (0.49)
Median | 12.4 | 0.0
Min, Max | 0, 25 | 0, 2
p-value of Wilcoxon rank sum test | <0.0001

Max=maximum, Min=minimum, SD=Standard deviation.

*Cumulative number of weeks of platelet response is defined as the total numbers of weeks in which the platelet count was ≥50×10^9/L during 6 months of treatment in the absence of rescue therapy.

In addition, a larger proportion of patients in the DOPTELET treatment group had platelet counts ≥50×10^9/L at Day 8 compared to placebo (21/32; 66% vs 0/17; 0.0%, respectively; p<0.0001).

14.3 Pediatric Patients with Persistent or Chronic Immune Thrombocytopenia

The efficacy and safety of DOPTELET was evaluated in pediatric patients ≥1 to <18 years of age with persistent or chronic immune thrombocytopenia in a randomized, double-blind, placebo-controlled trial (NCT 04516967), which included a 12-week randomized treatment phase (Core Phase).

Patients were required to have had a diagnosis of primary ITP for ≥6 months and had an insufficient response to at least one previous treatment, with an average of 2 baseline platelet counts less than 30×10^9/L. Patients (n=75) were randomized (3:1) to receive DOPTELET (n=54) or placebo (n=21). The starting dose for patients 6 years and older was 20 mg (tablet), while the starting dose for the youngest cohort was 10 mg (oral granules mixed with a soft food or liquid). Doses could be subsequently titrated based on platelet response.

Enrollment was 52% male and 48% female. The median age of patients receiving DOPTELET was 8.5 years (range 1 to 17) while the median age of patients receiving placebo was 10.0 years (range 3 to 17). Patients identified their race as White (84%), Asian (5.3%), and Other (5.3%); 5.3% did not report race. Patients identified their ethnicity as Not Hispanic or Latino (86.7%) and Hispanic or Latino (6.7%); 2.7% did not report ethnicity and 4% had unknown ethnicity.

The median baseline platelet counts were 10.4×10^9/L in the DOPTELET group and 11.5×10^9/L in the placebo group. The percentage of patients who had received 3 or more prior ITP therapies was 68.5% in the avatrombopag group and 66.7% in the placebo group. Most patients in the trial received at least one other TPO receptor agonist as a prior therapy (74.1% in the DOPTELET group and 71.4% in the placebo group).

The efficacy of DOPTELET in this trial was evaluated by durable platelet response, defined as the proportion of patients achieving at least 6 out of 8 weekly platelet counts ≥50×10^9/L during the last 8 weeks of the 12-week Treatment Period in the Core Phase in the absence of rescue medication (Table 15).

Efficacy was also evaluated by platelet response, defined as the proportion of subjects achieving at least 2 consecutive platelet assessments ≥50×10^9/L in the Core Phase in the absence of rescue medication.

Table 15: Durable Platelet Response and Platelet Response - Phase 3 Trial in Pediatric Patients with Persistent or Chronic ITP - Full Analysis Set

Endpoint | DOPTELET (N=54) | Placebo (N=21)
Durable platelet response, n%
Yes | 15 (27.8) |  | 0
No | 39 (72.2) |  | 21 (100.0)
Difference of proportion (avatrombopag – placebo) (95% CI) | 27.8 (15.8, 39.7)
CMH (avatrombopag vs. placebo) p-value | p=0.0077a
Platelet response, n%
Yes | 44 (81.5) |  | 0
No | 10 (18.5) |  | 21 (100.0)
Difference of proportion (avatrombopag – placebo) (95% CI) | 81.5 (71.1, 91.8)
CMH (avatrombopag vs. placebo) p-value | p <0.0001a

CI, Confidence interval; CMH, Cochran-Mantel-Haenszel; N, Total number of subjects; n, Number of subjects; Full Analysis Set includes all randomized subjects.

a Denotes p-value from Fisher’s Exact Test, which was used in place of CMH test due to sparse number of responders in the strata.

Note: The CMH test is adjusted for age cohort and baseline platelet counts.

DOPTELET was superior to placebo in other major efficacy outcomes that evaluated platelet counts. At Day 8, 55.6% (95% CI: 41.4%, 69.1%) of DOPTELET versus no placebo patients (95% CI: 0.0%, 16.1%) had a platelet count ≥50×10^9/L in the absence of rescue therapy (p <0.0001). The mean percentage of weeks that subjects had a platelet count ≥50×10^9/L during the Core Phase in the absence of rescue therapy was significantly higher for DOPTELET versus placebo, 48.9% (SD: 25.22%) versus 1.2% (SD: 3.92%) (p <0.0001).

The proportion of subjects who required rescue therapy during the Core Phase was significantly lower (p=0.0008) in the DOPTELET group (7.4% [95% CI: 2.1%, 17.9%]) than in the placebo group (42.9% [95% CI: 21.8%, 66.0%]).

16 HOW SUPPLIED/STORAGE AND HANDLING

16.1 DOPTELET Tablets

DOPTELET 20 mg tablets are supplied as round, biconvex, yellow, film-coated tablets, and debossed with “AVA” on one side and “20” on the other side.

How Supplied | Carton NDC | Blister Card NDC
Carton of one blister card with 10 tablets | NDC 71369-020-10 | NDC 71369-020-11
Carton of one blister card with 15 tablets | NDC 71369-020-15 | NDC 71369-020-16
Carton of two blister cards, each with 15 tablets (30 tablets total) | NDC 71369-020-30 | NDC 71369-020-16

Store DOPTELET tablets at room temperature from 20°C to 25°C (68°F to 77°F), excursions permitted from 15°C to 30°C (59°F to 86°F). Store tablets in the original package.

16.2 DOPTELET SPRINKLE

DOPTELET SPRINKLE is supplied as 10 mg capsules with a white opaque body and light blue opaque cap with a black arrow symbol imprinted on the body and cap. The capsule is filled with white to off-white granules.

How Supplied | Carton and Bottle NDC
Carton with one bottle of 30 capsules (containing oral granules) | NDC 71369-010-30

Store DOPTELET SPRINKLE capsules at room temperature from 20°C to 25°C (68°F to 77°F), excursions permitted from 15°C to 30°C (59°F to 86°F).

17 PATIENT COUNSELING INFORMATION

Advise the patient or caregiver to read the FDA-approved patient labeling: Patient Information and, for DOPTELET SPRINKLE, Instructions for Use.

Prior to treatment, patients should fully understand and be informed of the following risks and considerations for DOPTELET:

Risks

Thrombotic/Thromboembolic Complications

DOPTELET is a thrombopoietin (TPO) receptor agonist and TPO receptor agonists have been associated with thrombotic and thromboembolic complications in patients with chronic liver disease or immune thrombocytopenia. Portal vein thrombosis has been reported in patients with chronic liver disease treated with TPO receptor agonists. Various thromboembolic complications (arterial and venous) have been reported in patients treated with DOPTELET [see Warnings and Precautions (5.1)].

Drug Interactions

DOPTELET may be affected by other drugs and may require a dose adjustment when co-administered with other drugs; therefore, advise patients to report their use of any other prescription or nonprescription medications or dietary supplements [see Dosage and Administration (2.4 and 2.6), Drug Interactions (7)].

Pregnancy

Advise pregnant women of the potential risk to a fetus. Advise females of reproductive potential to inform their prescriber of a known or suspected pregnancy [see Use in Specific Populations (8.1)].

Lactation

Advise women not to breastfeed during treatment with DOPTELET and for at least 2 weeks after the last dose [see Use in Specific Populations (8.2)].

Administration Instructions for DOPTELET SPRINKLE

- Inform patients and caregivers to open the capsules and mix the contents with the recommended soft foods or liquids. Administer immediately after mixing. Do not swallow the capsules whole. Do not chew or crush the granules.
- Advise patients and caregivers to read and follow the Instructions for Use for DOPTELET SPRINKLE.

DOPTELET and DOPTELET SPRINKLE are not substitutable on a milligram-to-milligram basis

- Advise patients and caregivers that DOPTELET and DOPTELET SPRINKLE are not substitutable on a milligram-to-milligram basis.
- To avoid a dosing error from using the wrong dosage form, strongly advise patients and caregivers to visually inspect the product to verify the correct dosage form each time the prescription is filled.

DOPTELET is a registered trademark of AkaRx, Inc.

Manufactured for AkaRx, Inc., Morrisville, North Carolina 27560

©2025

For more information, go to www.DOPTELET.com or call 1-855-454-3887.

PI0002 R8

PATIENT INFORMATION

DOPTELET® (dop-TEL-et)

(avatrombopag) tablets, for oral use

DOPTELET® SPRINKLE (dop-TEL-et SPRINK-el)

(avatrombopag) oral granules

What are DOPTELET and DOPTELET SPRINKLE?

- DOPTELET is a prescription medicine used to treat low blood platelet counts in:
  - adults with long-lasting (chronic) liver disease (CLD) who are scheduled to have a medical or dental procedure.
  - adults with chronic immune thrombocytopenia (ITP) when other treatments have not worked well enough.
  - children 1 year and older with persistent or chronic ITP when other treatments have not worked well enough.

DOPTELET tablets and DOPTELET SPRINKLE are different dosage forms of DOPTELET. DOPTELET SPRINKLE is a capsule that contains granules that are mixed with a soft food or liquid for dosing.

DOPTELET tablets and DOPTELET SPRINKLE are not used to make platelet counts normal.

It is not known if DOPTELET tablets or DOPTELET SPRINKLE are safe and effective in children younger than 1 year of age.

Before you take DOPTELET or DOPTELET SPRINKLE, tell your healthcare provider about all of your medical conditions, including if you:

- have ever had a blood clot.
- are pregnant or plan to become pregnant. DOPTELET may harm your unborn baby. Tell your healthcare provider if you become pregnant or think you may be pregnant during treatment with DOPTELET.
- are breastfeeding or plan to breastfeed. It is not known if DOPTELET passes into your breast milk. Do not breastfeed during your treatment with DOPTELET and for at least 2 weeks after the last dose. Talk to your healthcare provider about the best way to feed your baby during this time.

Tell your healthcare provider about all of the medicines you take, including prescription and over-the-counter medicines, vitamins, and herbal supplements. DOPTELET or DOPTELET SPRINKLE may affect the way other medicines work, and other medicines may affect the way DOPTELET or DOPTELET SPRINKLE works.

How should I take DOPTELET?

- DOPTELET tablets that come in a blister package are not the same dosage form as DOPTELET SPRINKLE that come in a bottle and cannot be directly substituted for each other. Contact your or your child’s pharmacist or healthcare provider if you did not receive the correct dosage form.
- Take DOPTELET exactly as your healthcare provider tells you to take it.
- Your healthcare provider will tell you how much DOPTELET to take and when to start taking it.
- Your healthcare provider may change your dose of DOPTELET depending on your blood platelet counts.
- Take DOPTELET with food.
- If you take DOPTELET to treat your low blood platelet counts due to chronic liver disease before a medical or dental procedure, your healthcare provider will check your platelet count before treatment and on the day of your scheduled procedure.
- If you take DOPTELET to treat your low blood platelet counts due to persistent or chronic immune thrombocytopenia, your healthcare provider will check your platelet count before, during and for at least 4 weeks after stopping your treatment with DOPTELET.
- If you are taking DOPTELET before a scheduled medical procedure and you miss a dose, contact your healthcare provider for further dosing instructions.
- If you are taking DOPTELET for persistent or chronic immune thrombocytopenia and you miss a dose, take it as soon as you remember. Do not take 2 doses at one time to make up for a missed dose. Take your next dose at your usual scheduled time.
- If you take too much DOPTELET, call your healthcare provider or Poison Help Line at 1-800-222-1222, or go to the nearest hospital emergency room right away.

How should I give DOPTELET SPRINKLE?

- DOPTELET SPRINKLE oral granules that come in a bottle are not the same dosage form as DOPTELET tablets that come in a blister card and cannot be directly substituted for each other. Contact your child’s pharmacist or healthcare provider if you did not receive the correct dosage form.
- If your child is prescribed DOPTELET SPRINKLE: See the Instructions for Use on how to prepare and give a dose.
- Open the capsules and sprinkle the contents onto a small amount of a soft food or liquid. Mix or stir the granules into the soft food or liquid and take right away.
- Do not swallow the capsules whole or the empty capsule shells.
- Do not chew or crush the oral granules.
- Give DOPTELET SPRINKLE exactly as your child’s healthcare provider tells you to give it.
- Your child’s healthcare provider will tell you how much DOPTELET SPRINKLE to give and when to start taking it.
- Your child’s healthcare provider may change the dose of DOPTELET SPRINKLE.
- Give your child DOPTELET SPRINKLE with food.
- If your child is taking DOPTELET SPRINKLE to treat low blood platelet counts due to persistent or chronic immune thrombocytopenia, your child’s healthcare provider will check your child’s platelet count before, during and for at least 4 weeks after stopping treatment with DOPTELET SPRINKLE.
- If you are giving DOPTELET SPRINKLE for your child’s persistent or chronic immune thrombocytopenia and miss a dose, give it as soon as you remember. Do not give 2 doses at one time to make up for a missed dose. Give the next dose at the usual scheduled time.
- If your child takes too much DOPTELET SPRINKLE, call your child’s healthcare provider or Poison Help Line at
  1-800-222-1222 or go to the nearest hospital emergency room right away.

What are the possible side effects of DOPTELET or DOPTELET SPRINKLE?

DOPTELET or DOPTELET SPRINKLE may cause serious side effects, including:

Blood clots. People with chronic liver disease or persistent or chronic immune thrombocytopenia and people with certain blood clotting conditions may have an increased risk of developing blood clots. Tell your healthcare provider right away if you get signs and symptoms of a blood clot, including:

• swelling, pain, or tenderness in your legs • fast heartbeat

• shortness of breath • stomach (abdominal) pain or tenderness

• chest pain

The most common side effects of DOPTELET when used to treat low blood platelet counts in adults with chronic liver disease (CLD) who are scheduled to have a medical or dental procedure are:

• fever • headache

• stomach (abdominal) pain • tiredness

• nausea • swelling of hands or feet

The most common side effects of DOPTELETwhen used to treat low blood platelet counts in adults with chronic immune thrombocytopenia (ITP) are:

• headache • joint pain

• tiredness • bleeding gums

• bruising • purple or red spots on your skin

• nosebleed • runny nose

• upper respiratory infection

The most common side effects of DOPTELETor DOPTELET SPRINKLEwhen used to treat low blood platelet counts in children 1 year and older with persistent or chronic immune thrombocytopenia (ITP) are:

• viral infection • fever

• runny nose • pain in the mouth or throat

• cough

These are not all of the possible side effects of DOPTELET or DOPTELET SPRINKLE.

Call your doctor for medical advice about side effects. You may report side effects to FDA at 1-800-FDA-1088.

How should I store DOPTELET tablets or DOPTELET SPRINKLE?

- Store DOPTELET tablets or DOPTELET SPRINKLE at room temperature from 68°F to 77°F (20°C to 25°C).
- Store DOPTELET tablets in the original package.

Keep DOPTELET tablets, DOPTELET SPRINKLE and all medicines out of the reach of children.

General information about the safe and effective use of DOPTELET or DOPTELET SPRINKLE.

Medicines are sometimes prescribed for purposes other than those listed in a Patient Information leaflet. Do not use DOPTELET or DOPTELET SPRINKLE for a condition for which it was not prescribed. Do not give DOPTELET tablets or DOPTELET SPRINKLE to other people, even if they have the same symptoms that you have. It may harm them. You can ask your pharmacist or healthcare provider for information about DOPTELET or DOPTELET SPRINKLE that is written for health professionals.

What are the ingredients in DOPTELET tablets or DOPTELET SPRINKLE?

Active ingredient: avatrombopag

Inactive ingredients in DOPTELET tablets: colloidal silicon dioxide, crospovidone, lactose monohydrate, magnesium stearate and microcrystalline cellulose. Tablet coating film: ferric oxide yellow, polyethylene glycol, polyvinyl alcohol, talc, and titanium dioxide.

Inactive ingredients in DOPTELET SPRINKLE: crospovidone Type A, magnesium stearate, mannitol, microcrystalline cellulose, and sodium lauryl sulfate. Capsule shells: Hypromellose.

DOPTELET is a registered trademark of AkaRx, Inc.

Manufactured for AkaRx, Inc., Morrisville, North Carolina 27560

For more information, go to www.DOPTELET.com or call 1-855-454-3887.

This Patient Information has been approved by the U.S. Food and Drug Administration. Revised: 07/2025 PI0001 R8

INSTRUCTIONS FOR USE

DOPTELET® SPRINKLE (dop-TEL-et SPRINK-el)

(avatrombopag) oral granules

Read these Instructions for Use to prepare and give a dose of DOPTELET SPRINKLE correctly.

- Important information that you need to know before giving DOPTELET SPRINKLE:

The contents of DOPTELET SPRINKLE should be sprinkled onto a soft food or liquid, as described below.

- DOPTELET SPRINKLE that comes in a bottle is not the same dosage form as DOPTELET tablets that come in a blister card and these products cannot be directly substituted for each other. Contact your child’s pharmacist or healthcare provider if your child did not receive the correct dosage form.
- DOPTELET SPRINKLE contains granules inside of a capsule.
  - The capsule must be opened, and the granules inside must be sprinkled onto a soft food or liquid to give a dose of DOPTELET SPRINKLE.
  - Do not swallow the capsule whole or the empty capsule shells.
  - Do not chew or crush the granules.
- Use all of the granules in the capsule. Do not use part of a capsule to try to prepare a dose.

Steps to prepare and give a dose of DOPTELET SPRINKLE:

1. Gather supplies to prepare a dose of DOPTELET SPRINKLE: capsule(s), liquid or soft food, cup or spoon, and mixing utensil (e.g., stir stick or small spoon); then wash your hands.
2. Put a small amount of soft food or liquid in a cup or spoon. The following soft foods and liquids can be used:

Soft foods

- applesauce
- strawberry jelly
- yogurt (plain)

Liquids

- milk (whole or skim)
- orange juice
- pediatric electrolyte solution (unflavored)
- water

3. Carefully open the capsule (or 2 capsules if prescribed) by pulling it apart.

- Sprinkle the entire contents of the capsule onto the soft food or liquid that you put in the spoon or cup. Make sure that all of the granules from the capsule have been completely emptied.

4. Mix or stir the granules into the soft food or liquid. The granules will not dissolve.
5. Give the mixture right away; do not save for later use.
6. Rinse the spoon or cup with additional soft food or liquid to make sure that the entire dose is given.
7. Throw the empty capsule shells away in the trash.

How should I store DOPTELET SPRINKLE?

- Store DOPTELET SPRINKLE at room temperature from 68°F to 77°F (20°C to 25°C).

Keep DOPTELET SPRINKLE and all medicines out of the reach of children.

DOPTELET is a registered trademark of AkaRx, Inc.

Manufactured for AkaRx, Inc., Morrisville, North Carolina 27560

For more information, go to www.DOPTELET.com or call 1-855-454-3887.

This Instructions for Use has been approved by the U.S. Food and Drug Administration. Issued: 07/2025 PI0003 R1

PRINCIPAL DISPLAY PANEL

NDC 71369-020-10
20 mg per tablet
Rx Only
Doptelet
one blister card with 10 tablets

PRINCIPAL DISPLAY PANEL

NDC 71369-020-15
20 mg per tablet
Rx Only
Doptelet
one blister card with 15 tablets

PRINCIPAL DISPLAY PANEL

NDC 71369-020-30
20 mg per tablet
Rx Only
Doptelet
Two blister cards with 15 tablets each (30 tablets)

PRINCIPAL DISPLAY PANEL

NDC 71369-010-30
10 mg per capsule
Rx Only
Doptelet Sprinkle

one bottle with 30 capsules